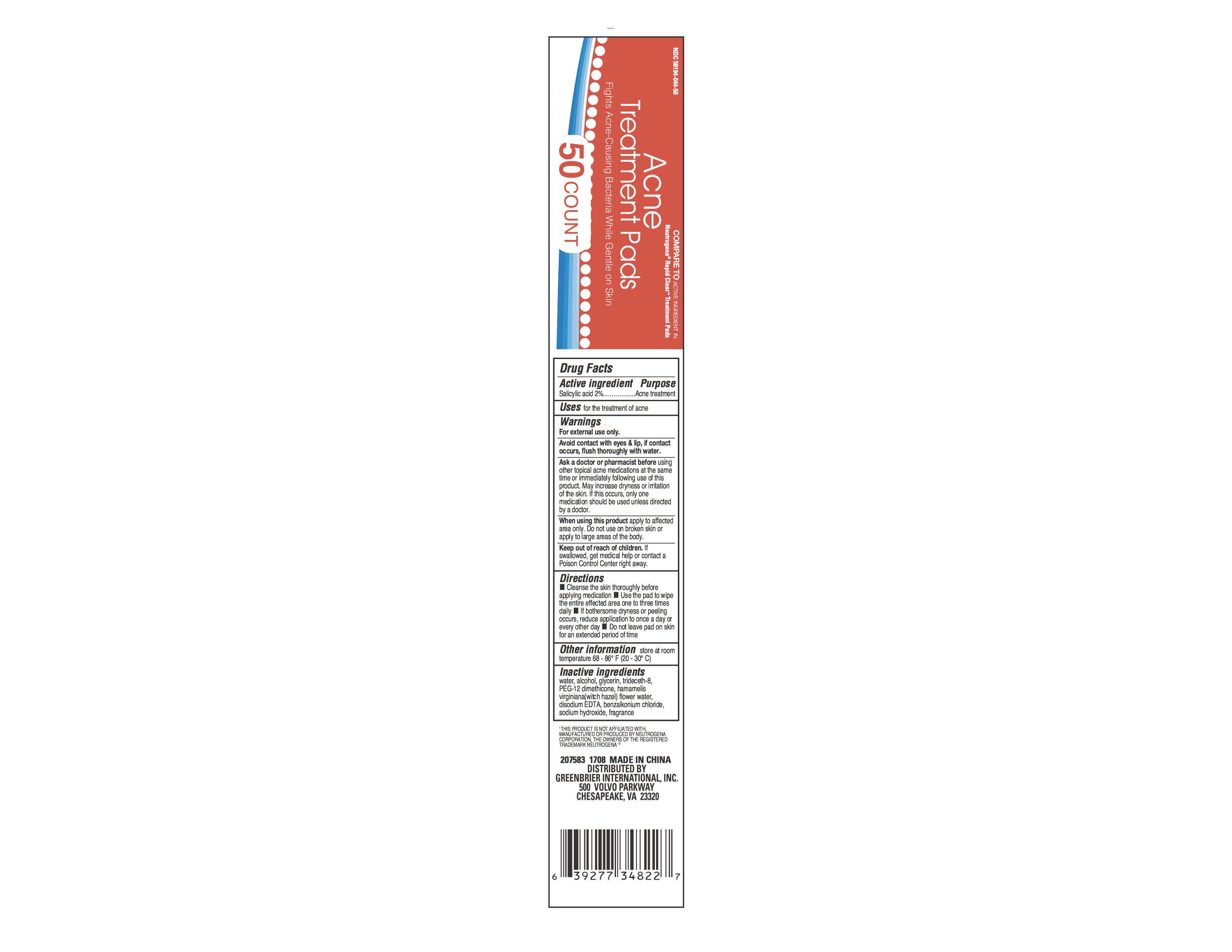 DRUG LABEL: Acne Treatment Pads
NDC: 71537-001 | Form: PATCH
Manufacturer: Huijing (Shanghai) Bio-tech Co., Ltd
Category: otc | Type: HUMAN OTC DRUG LABEL
Date: 20170623

ACTIVE INGREDIENTS: SALICYLIC ACID 2 g/100 mL
INACTIVE INGREDIENTS: WATER; ALCOHOL; GLYCERIN; TRIDECETH-8; PEG-12 DIMETHICONE; HAMAMELIS VIRGINIANA FLOWER WATER; EDETATE DISODIUM; BENZALKONIUM CHLORIDE; SODIUM HYDROXIDE

Active ingredient

Salicylic acid 2%

Purpose

Acne treatment

INDICATIONS AND USAGE

Uses for the treatment of acne

Warnings

For external use only.

Avoid contact with eyes & lip, if contact

occurs, flush throoughly with water.

Ask a doctor or pharmacist before using

other topical acne medications at the same time

or immediately following use of this product. May increase

dryness or irritation of the skin. If this occurs, only one

medication should be usedunless directed

by a doctor.

When using this product apply to affected

area only. Do not use on broken skin or

apply to large areas of the body.

Keep out of reach of children. If

swallowed, get medical help or contact a

Poison Control Center right away.

Directions

•Cleanse the skin thoroughly before applying medication

•Use the pad to wipe the entire affected area one to three times daily

•If bothersome dryness or peeling occurs, reduce application to once a day or every other day

Do not peave pad on skin for an extended period of time.

Other information store at room

temperature 68 - 86 F (20 - 30 C)

Inactive ingredients water,

alcohol, glycerin, trideceth - 8,

PEG-12 dimethicone, hamamelis virginiana

(witch hazel) flower water, disodium EDTA,

benzalkonium chloride, sodium hydroxide,

fragrance